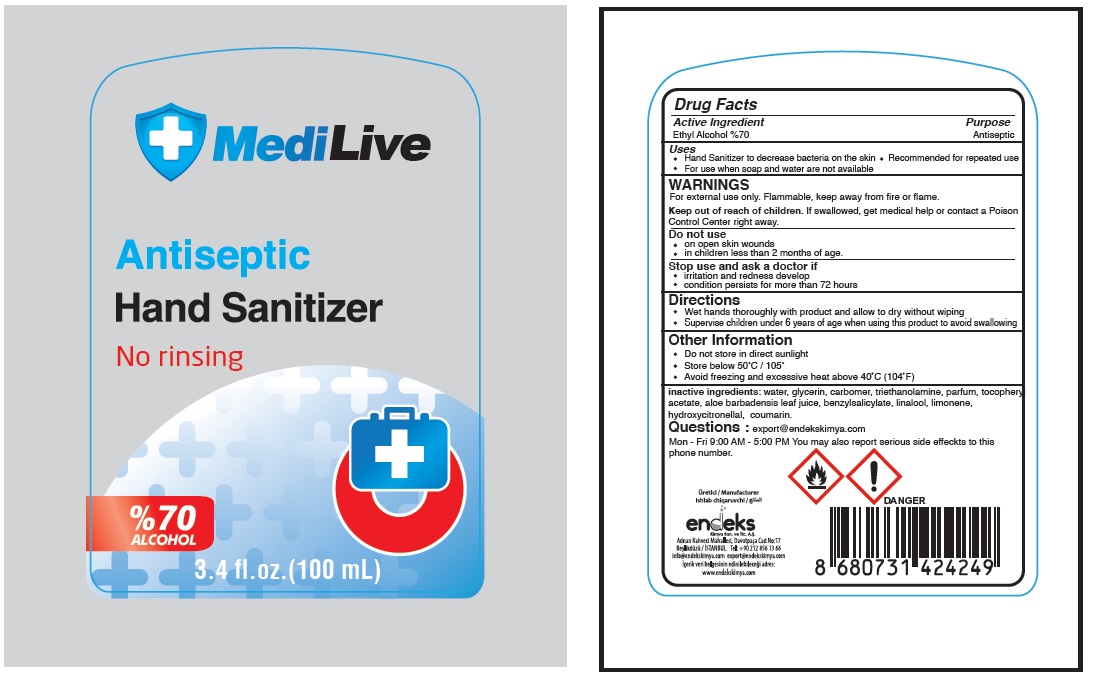 DRUG LABEL: MediLive
NDC: 78089-026 | Form: GEL
Manufacturer: Endeks Kimya Sanayi Ve Ticaret Anonim Sirketi
Category: otc | Type: HUMAN OTC DRUG LABEL
Date: 20200602

ACTIVE INGREDIENTS: ALCOHOL 70 mL/100 mL
INACTIVE INGREDIENTS: WATER; GLYCERIN; CARBOMER HOMOPOLYMER, UNSPECIFIED TYPE; TROLAMINE; .ALPHA.-TOCOPHEROL ACETATE; ALOE VERA LEAF; BENZYL SALICYLATE; LINALOOL, (+/-)-; LIMONENE, (+)-; HYDROXYCITRONELLAL; COUMARIN

MediLive Antiseptic Hand Sanitizer

Active Ingredient

Ethyl Alcohol 70%

Purpose

Antiseptic

Uses

• Hand Sanitizer to decrease bacteria on the skin • Recommended for repeated use • For use when soap and water are not available

WARNINGS

For external use only. Flammable, keep away from fire or flame.

Do not use

- on open skin wounds
- in children less than 2 months of age.

Stop use and ask a doctor if

- irritation and redness develop
- condition persists for more than 72 hours

Keep out of reach of children. If swallowed, get medical help or contact a Poison Control Center right away.

Directions

- Wet hands thoroughly with product and allow to dry without wiping
- Supervise children under 6 years of age when using this product to avoid swallowing

Other Information

- Do not store in direct sunlight
- Store below 50°C / 105°F
- Avoid freezing and excessive heat above 40°C (104°F)

INACTIVE INGREDIENT

Inactive Ingredients: water, glycerin, carbomer, triethanolamine, parfum, tocopheryl acetate, aloe barbadensis leaf juice, benzylsalicylate, linalool, limonene, hydroxycitronellal, coumarin.

Questions : export@endekskimya.com

Mon - Fri 9:00 AM - 5:00 PM You may also report serious side effects to this phone number

No rinsing

%70 ALCOHOL

Uretici / Manufacturer

Ishlab chiqaruvchi /

endeks

Kimya San. ve Tic A.S.

Adnan Kahveci Mahallesi, Davutpasa Cad.No:17

Beylikdüzü / ISTANBUL Tel: +90 212 856 13 66

info@endekskimya.com export@endekskimya.com

Icerik veri belgesinin edinilebilecegi adres:

www.endekskmya.com